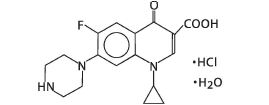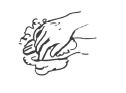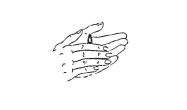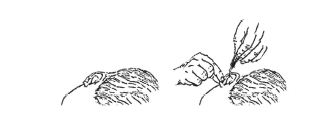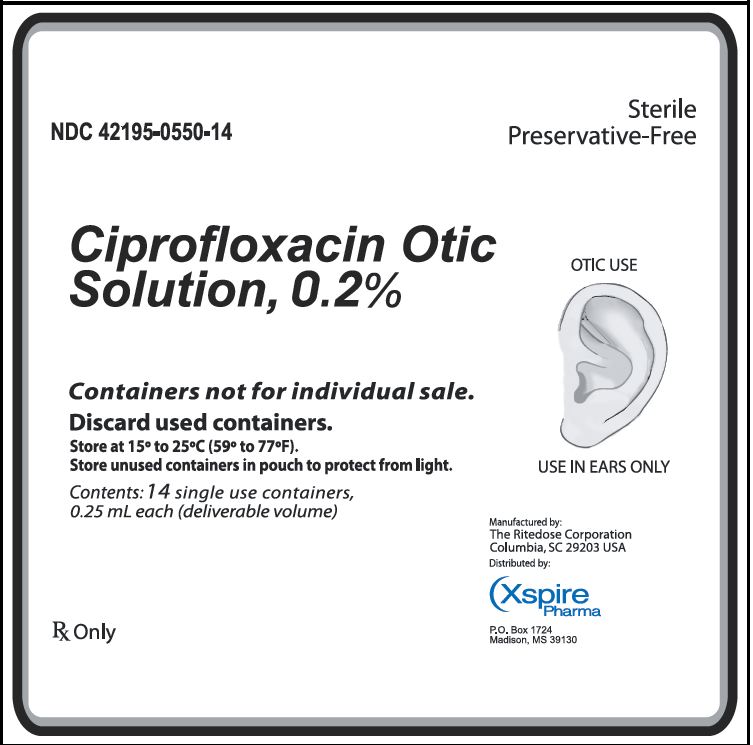 DRUG LABEL: Ciprofloxacin Otic
NDC: 42195-550 | Form: SOLUTION/ DROPS
Manufacturer: Xspire Pharma, Llc
Category: prescription | Type: HUMAN PRESCRIPTION DRUG LABEL
Date: 20241009

ACTIVE INGREDIENTS: CIPROFLOXACIN HYDROCHLORIDE 0.5 mg/0.25 mL
INACTIVE INGREDIENTS: POVIDONE, UNSPECIFIED; GLYCERIN; WATER

HIGHLIGHTS OF PRESCRIBING INFORMATION

THESE HIGHLIGHTS DO NOT INCLUDE ALL THE INFORMATION NEEDED TO USE CIPROFLOXACIN OTIC SOLUTION SAFELY AND EFFECTIVELY. SEE FULL PRESCRIBING INFORMATION FOR CIPROFLOXACIN OTIC SOLUTION.
Ciprofloxacin Otic Solution, 0.2%
Initial U.S. Approval: 1987

1 INDICATIONS AND USAGE

Ciprofloxacin Otic Solution is a quinolone antimicrobial indicated for the treatment of acute otitis externa due to susceptible isolates of Pseudomonas aeruginosaor Staphylococcus aureus. (1)

2 DOSAGE AND ADMINISTRATION

Contents of one single use container should be instilled into the affected ear twice daily (approximately 12 hours apart) for 7 days. (2)

3 DOSAGE FORMS AND STRENGTHS

Ciprofloxacin Otic Solution is a sterile, preservative-free otic solution of ciprofloxacin hydrochloride equivalent to 0.2 % ciprofloxacin (0.5 mg in 0.25 mL) in each single use container. (3)

4 CONTRAINDICATIONS

History of hypersensitivity to ciprofloxacin. (4)

5 WARNINGS AND PRECAUTIONS

- Ciprofloxacin Otic Solution is for otic use only. (5.1)
- Hypersensitivity: discontinue at the first appearance of a skin rash or any other sign of hypersensitivity. (5.2)
- Use of Ciprofloxacin Otic Solution may result in overgrowth of nonsusceptible organisms. (5.3)

6 ADVERSE REACTIONS

The most common adverse reactions reported in 2-3% of patients treated with Ciprofloxacin Otic Solution were application site pain, ear pruritus, fungal ear superinfection, and headache. (6)

To report SUSPECTED ADVERSE REACTIONS, contact Xspire Pharma at 1-888-252-3901 or FDA at 1-800-FDA-1088 or www.fda.gov/medwatch.

FULL PRESCRIBING INFORMATION

1 INDICATIONS AND USAGE

Ciprofloxacin Otic Solution is a quinolone antimicrobial indicated for the treatment of acute otitis externa due to susceptible isolates of Pseudomonas aeruginosaor Staphylococcus aureus.

2 DOSAGE AND ADMINISTRATION

The contents of one single use container (deliverable volume: 0.25 mL) should be instilled into the affected ear twice daily (approximately 12 hours apart) for 7 days.

Wash hands before use. The solution should be warmed, by holding the container in the hands for at least 1 minute, to minimize the dizziness that may result from the instillation of a cold solution into the ear canal. The patient should lie with the affected ear upward and then the solution should be instilled. This position should be maintained for at least 1 minute to facilitate penetration of the drops into the ear. Repeat, if necessary, for the opposite ear.

3 DOSAGE FORMS AND STRENGTHS

Ciprofloxacin Otic Solution is a sterile, preservative-free, otic solution of ciprofloxacin hydrochloride equivalent to 0.2 % ciprofloxacin (0.5 mg in 0.25 mL) in each single use container.

4 CONTRAINDICATIONS

Ciprofloxacin Otic Solution is contraindicated in persons with a history of hypersensitivity to ciprofloxacin.

5 WARNINGS AND PRECAUTIONS

5.1 Otic Use Only

Ciprofloxacin Otic Solution is for otic use only. It should not be used for injection, for inhalation or for topical ophthalmic use.

5.2 Hypersensitivity

Ciprofloxacin Otic Solution should be discontinued at the first appearance of a skin rash or any other sign of hypersensitivity.

5.3 Growth of Resistant Organisms with Prolonged Use

As with other anti-infectives, use of Ciprofloxacin Otic Solution may result in overgrowth of nonsusceptible organisms, including yeast and fungi. If super-infection occurs, discontinue use and institute alternative therapy.

5.4 Lack of Clinical Response

If the infection is not improved after one week of therapy, cultures may help guide further treatment.

6 ADVERSE REACTIONS

Because clinical studies are conducted under widely varying conditions, adverse drug reaction rates observed in the clinical studies of a drug cannot be directly compared to rates in the clinical studies of another drug and may not reflect the rates observed in clinical practice.

In a randomized, active-controlled clinical trial, approximately 300 patients with clinical signs and symptoms of otitis externa were treated with Ciprofloxacin Otic Solution. The most frequently reported adverse reactions were application site pain, ear pruritus, fungal ear superinfection, and headache, each reported in approximately 2-3% of patients.

8 USE IN SPECIFIC POPULATIONS

8.1 Pregnancy

Pregnancy Category C.

Reproduction studies have been performed in rats and mice using oral doses of up to 100 mg/kg and intravenous (IV) doses up to 30 mg/kg and have revealed no evidence of harm to the fetus as a result of ciprofloxacin. In rabbits, ciprofloxacin (30 and 100 mg/kg orally) produced gastrointestinal disturbances resulting in maternal weight loss and an increased incidence of abortion, but no teratogenicity was observed at either dose. After intravenous administration of doses up to 20 mg/kg, no maternal toxicity was produced in the rabbit, and no embryotoxicity or teratogenicity was observed.

Animal reproduction studies have not been conducted with Ciprofloxacin Otic Solution. No adequate and well-controlled studies have been performed in pregnant women. Caution should be exercised when Ciprofloxacin Otic Solution is used by a pregnant woman.

8.3 Nursing Mothers

Ciprofloxacin is excreted in human milk with systemic use. It is not known whether ciprofloxacin is excreted in human milk following otic use. Because of the potential for serious adverse reactions in nursing infants, a decision should be made whether to discontinue nursing or to discontinue the drug, taking into account the importance of the drug to the mother.

8.4 Pediatric Use

The safety and effectiveness of Ciprofloxacin Otic Solution in infants below one year of age have not been established. The efficacy of Ciprofloxacin Otic Solution in treating otitis externa in pediatric patients one year or older has been demonstrated in controlled clinical trials (see Section 14 Clinical Studies).

There is no evidence that the otic administration of quinolones has any effect on weight bearing joints, even though systemic administration of some quinolones has been shown to cause arthropathy in immature animals.

8.5 Geriatric Use

No overall differences in safety and effectiveness have been observed between elderly and younger patients.

11 DESCRIPTION

Ciprofloxacin Otic Solution 0.2% contains the synthetic antimicrobial agent ciprofloxacin hydrochloride. Ciprofloxacin Otic Solution is a sterile, preservative-free solution for otic use. Each single use container of Ciprofloxacin Otic Solution delivers 0.25 mL of solution equivalent to 0.5 mg of ciprofloxacin. The inactive ingredients are povidone, glycerin, and water for injection. Sodium hydroxide and/or lactic acid may be added to adjust pH.

Ciprofloxacin, a fluroquinolone is available as the monohydrochloride, monohydrate salt of 1-cyclopropyl-6-fluoro-1,4-dihydro-4-oxo-7-(1-piperazinyl)-3-quinolinecarboxylic acid. Its molecular formula is C17H18FN3O3•HCl•H2O, and molecular weight is 385.82.

The chemical structure of ciprofloxacin hydrochloride is:

12 CLINICAL PHARMACOLOGY

12.1 Mechanism of Action

Ciprofloxacin is a fluoroquinolone antimicrobial (see 12.4 Clinical Pharmacology, Microbiology).

12.3 Pharmacokinetics

The plasma concentrations of ciprofloxacin were not measured following administration of 0.25 mL Ciprofloxacin Otic Solution (total dose: 0.5 mg ciprofloxacin). However, the maximum plasma concentration of ciprofloxacin is anticipated to be less than 5 ng/mL.

12.4 Microbiology

The bactericidal action of ciprofloxacin results from interference with the enzyme DNA gyrase, which is needed for the synthesis of bacterial DNA.

Bacterial resistance to quinolones can develop through chromosomally- or plasmid-mediated mechanisms.

The mechanism of action of fluoroquinolones, including ciprofloxacin, is different from that of macrolides. Therefore, ciprofloxacin may be active against pathogens that are resistant to these antibiotics, and these antibiotics may be active against pathogens that are resistant to ciprofloxacin. In vitrostudies demonstrated cross-resistance between ciprofloxacin and some fluoroquinolones.

Ciprofloxacin has been shown to be active against most isolates of the following bacteria, both in vitroand in clinical infections of acute otitis externa as described in Section 1 Indications and Usage.

- Staphylococcus aureus
- Pseudomonas aeruginosa.

13 NON-CLINICAL TOXICOLOGY

13.1 Carcinogenesis, Mutagenesis, and Impairment of Fertility

Long-term carcinogenicity studies in mice and rats have been completed for ciprofloxacin. After daily oral doses of 750 mg/kg (mice) and 250 mg/kg (rats) were administered for up to 2 years, there was no evidence that ciprofloxacin had any carcinogenic or tumorigenic effects in these species. No long-term studies of Ciprofloxacin Otic Solution have been performed to evaluate carcinogenic potential.

Eight in vitromutagenicity tests have been conducted with ciprofloxacin, and the test results are listed below:

- Salmonella/Microsome Test (Negative)
- Escherichia coliDNA Repair Assay (Negative)
- Mouse Lymphoma Cell Forward Mutation Assay (Positive)
- Chinese Hamster V79 Cell HGPRT Test (Negative)
- Syrian Hamster Embryo Cell Transformation Assay (Negative)
- Saccharomyces cerevisiaePoint Mutation Assay (Negative)
- Saccharomyces cerevisiaeMitotic Crossover and Gene Conversion Assay (Negative)
- Rat Hepatocyte DNA Repair Assay (Positive).

Two of the 8 in vitrotests were positive, but results of the following 3 in vivotest systems gave negative results:

- Rat Hepatocyte DNA Repair Assay
- Micronucleus Test (Mice)
- Dominant Lethal Test (Mice).

Fertility studies performed in rats at oral doses of ciprofloxacin up to 100 mg/kg/day revealed no evidence of impairment. This would be over 100 times the maximum recommended clinical dose of ototopical ciprofloxacin based upon body surface area, assuming total absorption of ciprofloxacin from the ear of a patient treated with Ciprofloxacin Otic Solution twice per day.

14 CLINICAL STUDIES

In a randomized, multi-center, evaluator-blinded study of patients with acute otitis externa, patients were treated with either Ciprofloxacin Otic Solution twice daily or neomycin and polymyxin B sulfates and hydrocortisone otic solution (PNH) three times daily for 7 days.

In the per protocol population, clinical cure was achieved at the end of a 7-day treatment in 70% (173/247) for the Ciprofloxacin Otic Solution treated group versus 60% (147/243) for the control treated group.

16 HOW SUPPLIED/STORAGE AND HANDLING

Ciprofloxacin Otic Solution is a clear, colorless, sterile, preservative-free solution. Ciprofloxacin Otic Solution is supplied as a 0.2% otic solution in a low-density polyethylene (LDPE) single use container. Each single use container delivers 0.25 mL of solution equivalent to 0.5 mg of ciprofloxacin; 14 single use containers are packaged in a foil overwrap pouch in a carton (NDC 42195-550-14).

STORAGE AND HANDLING

Store at 15ºC to 25ºC (59ºF to 77ºF). Discard used containers. Store unused containers in pouch to protect from light.

17 PATIENT COUNSELING INFORMATION

17.1 Directions for Use

Patients should be advised that Ciprofloxacin Otic Solution is for otic use only. It is not for ophthalmic or inhalation use. It is not for injection.

Ciprofloxacin Otic Solution should be given 2 times each day (about 12 hours apart) in each infected ear.

Ciprofloxacin Otic Solution should be used for as long as it is prescribed, even if the symptoms improve. The patient should be advised to follow these directions while on Ciprofloxacin Otic Solution:

- Wash their hands before use.
- Warm the container in their hands for at least one minute prior to use to minimize dizziness that may result from the instillation of a cold solution into the ear canal. Twist off and discard top of container.
- Lie with the affected ear upward and then instill the contents of one container into the ear. Maintain this position for at least one minute to facilitate penetration of the drops into the ear.
- Repeat, if necessary, for the opposite ear.
- Discard used container.
- Store unused containers in pouch to protect from light.

17.2 Hypersensitivity

Patients should be advised to immediately discontinue Ciprofloxacin Otic Solution at the first appearance of a skin rash or any other sign of hypersensitivity [see Section 5.1 Warnings and Precautions].

Ciprofloxacin Otic Solution is:
Distributed by:
Xspire Pharma
P.O. Box 1724
Madison, MS 39130.

Manufactured by:
The Ritedose Corporation
Columbia, SC 29203 USA

PRINCIPAL DISPLAY PANEL - 0.25 mL

Sterile
Preservative-Free

NDC 42195-0550-14

Ciprofloxacin Otic
Solution, 0.2%

Containers not for individual sale.

Discard used containers.

Store at 15ºC to 25ºC (59ºF to 77ºF).
Store unused containers in pouch to protect from light.

Contents: 14 single use containers
0.25 ml each (deliverable volume)

RxOnly

Manufactured by:
The Ritedose Corporation
Columbia, SC 29203 USA

(Xspire
Pharma

P.O. Box 1724
Madison, MS 39130